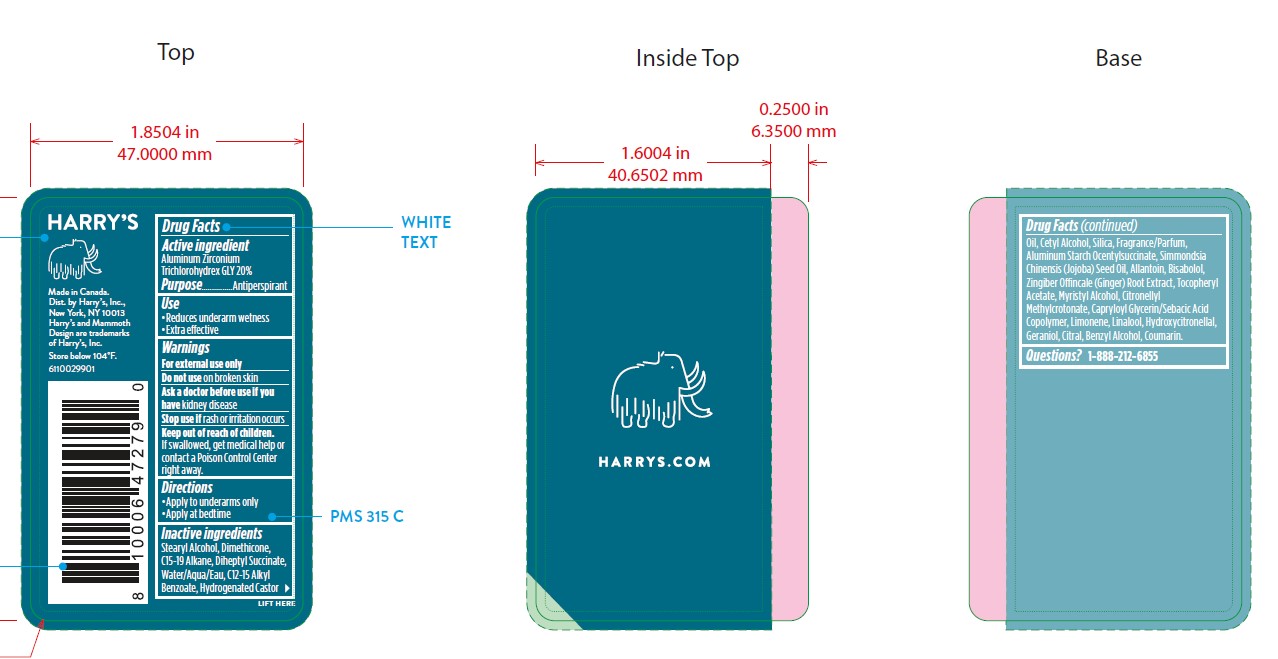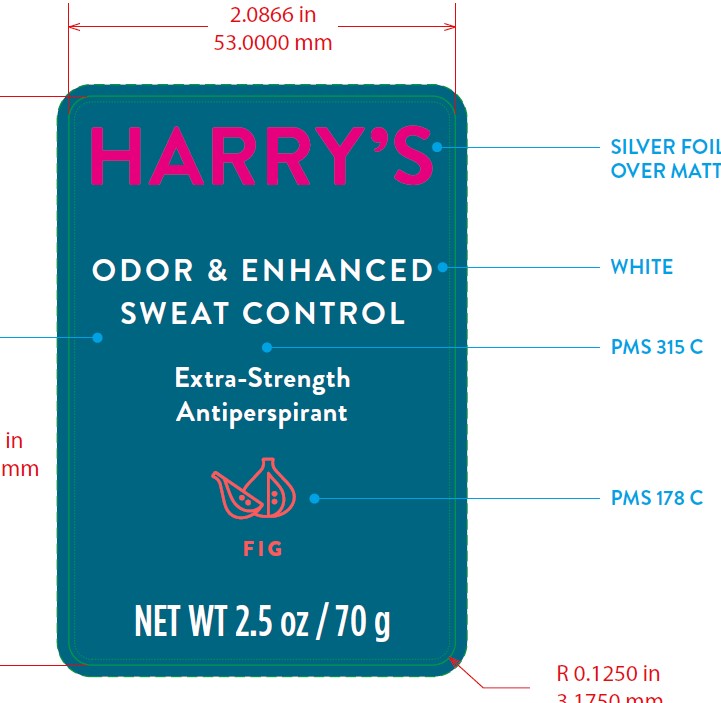 DRUG LABEL: Harrys Extra Strength Antiperspirant Fig
NDC: 70533-012 | Form: STICK
Manufacturer: Harry's Inc.
Category: otc | Type: HUMAN OTC DRUG LABEL
Date: 20221222

ACTIVE INGREDIENTS: ALUMINUM ZIRCONIUM TRICHLOROHYDREX GLY 200 mg/1 g
INACTIVE INGREDIENTS: STEARYL ALCOHOL; HYDROGENATED CASTOR OIL; ALUMINUM STARCH OCTENYLSUCCINATE; JOJOBA OIL; GINGER; .ALPHA.-TOCOPHEROL ACETATE; .ALPHA.-BISABOLOL, (+/-)-; CITRONELLYL METHYLCROTONATE; LIMONENE, (+/-)-; LINALOOL, (+/-)-; COUMARIN; BENZYL ALCOHOL; ALLANTOIN; GERANIOL; CITRAL; HYDROXYCITRONELLAL; ALKYL (C12-15) BENZOATE; DIMETHICONE; WATER; CETYL ALCOHOL; SILICON DIOXIDE; MYRISTYL ALCOHOL; DIHEPTYL SUCCINATE; C15-19 ALKANE; FRAGRANCE 13576; CAPRYLOYL GLYCERIN/SEBACIC ACID COPOLYMER (2000 MPA.S)

Extra Strength AP - Fig

Active Ingredient

ALUMINUM ZIRCONIIUM TRICHLOROHYDREX GLY 20%

Purpose

Antiperspirant

Use

Reduces underarm wetness.
Extra effective

Warnings

For external use only

Do not use on broken skin

Ask doctor before use if you have kidney disease

Stop use if rash or irritation occurs.

Keep out of reach of children. If swallowed, get medical help or contact a Poison Control Center right away.

Directions

Apply to underarms only
Apply at bedtime

Inactive Ingredients

STEARYL ALCOHOL, DIMETHICONE, C15-19 ALKANE, DIHEPTYL SUCCINATE, WATER/AQUA/EAU, C12-15 ALKYL BENZOATE, HYDROGENATED CASTOR OIL, CETYL ALCOHOL, SILICA, FRAGRANCE/PARFUM, ALUMINUM STARCH OCENTYLSUCCINATE, SIMMONDSIA CHINENSIS (JOJOBA) SEED OIL, ALLANTOIN, BISABOLOL, ZINGIBER OFFINCALE (GINGER) ROOT EXTRACT, TOCOPHERYL ACETATE, MYRISTYL ALCOHOL, CITRONELLYL METHYLCROTONATE, CAPRYLOYL GLYCERIN/SEBACIC ACID COPOLYMER, LIMONENE, LINALOOL, HYDROXYCITRONELLAL, GERANIOL, CITRAL, BENZYL ALCOHOL, COUMARIN.

Questions?: 1-888-212-6855

PACKAGE LABEL

NDC 70533-012-25